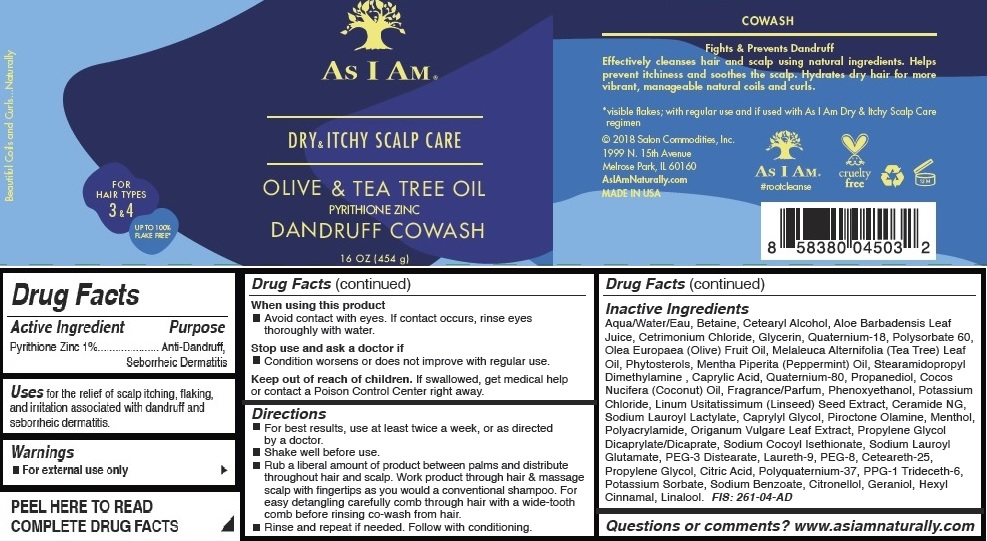 DRUG LABEL: As I Am
NDC: 72474-103 | Form: EMULSION
Manufacturer: Salon Commodities, Inc.
Category: otc | Type: HUMAN OTC DRUG LABEL
Date: 20241009

ACTIVE INGREDIENTS: PYRITHIONE ZINC 10 mg/1 g
INACTIVE INGREDIENTS: CETRIMONIUM CHLORIDE; PROPYLENE GLYCOL DICAPRYLATE/DICAPRATE; PHENOXYETHANOL; .BETA.-SITOSTEROL; POLYACRYLAMIDE (10000 MW); MENTHOL; PROPYLENE GLYCOL; PPG-1 TRIDECETH-6; OREGANO; CITRIC ACID MONOHYDRATE; .BETA.-CITRONELLOL, (R)-; .ALPHA.-HEXYLCINNAMALDEHYDE; CAPRYLYL GLYCOL; POLYSORBATE 60; QUATERNIUM-18; PROPANEDIOL; POTASSIUM CHLORIDE; WATER; ALOE VERA LEAF; COCONUT OIL; GERANIOL; LINALOOL, (+/-)-; CETOSTEARYL ALCOHOL; BETAINE; GLYCERIN; OLIVE OIL; TEA TREE OIL; PEPPERMINT OIL; POLIDOCANOL; STEARDIMONIUM HYDROXYPROPYL PEG-7 DIMETHICONE PHOSPHATE CHLORIDE; CERAMIDE NG; CETEARETH-25; POTASSIUM SORBATE; SODIUM LAUROYL LACTYLATE; SODIUM COCOYL ISETHIONATE; SODIUM LAUROYL GLUTAMATE; PEG-3 DISTEARATE; POLYETHYLENE GLYCOL 400; SODIUM BENZOATE; POLYQUATERNIUM-37 (10000 MPA.S); LINSEED OIL; PIROCTONE OLAMINE; STEARAMIDOPROPYL DIMETHYLAMINE; CAPRYLIC ACID

As I Am - Dry & Itchy Scalp Care - Olive and Tea Tree Oil Co-Wash

Active Ingredient

Zinc Pyrithione 1%

Purpose

Anti-Dandruff, Seborrheic Dermatitis

Uses

For the relief of scalp itching, flaking, and irritation associated with dandruff and seborrheic dermatitis.

Warnings

- For external use only.

When Using This Product

- Avoid contact with eyes. If contact occurs, rinse eyes thoroughly with water.

Stop use and ask a doctor if

- Condition worsens or does not improve with regular use.

Keep out of reach of children. If swallowed, get medical help or contact a Poison Control Center right away.

Directions

- For best results, use at least twice a week, or as directed by a doctor.
- Shake well before use.
- Rub a liberal amount of product between palms and distribute throughout hair and scalp. Work product through hair & massage scalp with fingertips as you would a conventional shampoo. For easy detangling carefully comb through hair with a wide-tooth comb before rinsing co-wash from hair.
- Rinse and repeat if needed. Follow with conditioning.

Inactive Ingredient

Aqua/Water/Eau, Betaine, Cetearyl Alcohol, Aloe Barbadensis Leaf

Juice, Cetrimonium Chloride, Glycerin, Quaternium-18, Polysorbate 60,

Olea Europaea (Olive) Fruit Oil, Melaleuca Alternifolia (Tea Tree) Leaf

Oil, Phytosterols, Mentha Piperita (Peppermint) Oil, Stearamidopropyl

Dimethylamine,Caprylic Acid, Quaternium-80, Propanediol, Cocos

Nucifera (Coconut) Oil, Fragrance/Parfum, Phenoxyethanol, Potassium

Chloride, Linum Usitatissimum (Linseed) Seed Extract, Ceramide NG,

Sodium Lauroyl Lactylate, Caprylyl Glycol, Piroctone Olamine, Menthol,

Polyacrylamide, Origanum Vulgare Leaf Extract, Propylene Glycol

Dicaprylate/Dicaprate, Sodium Cocoyl Isethionate, Sodium Lauroyl

Glutamate, PEG-3 Distearate, Laureth-9, PEG-8, Ceteareth-25,

Propylene Glycol, Citric Acid, Polyquaternium-37, PPG-1 Trideceth-6,

Potassium Sorbate, Sodium Benzoate, Citronellol, Geraniol, Hexyl

Cinnamal, Linalool.

Questions or comments? www.asiamnaturally.com

PACKAGE LABEL

As I Am - Dry & Itchy Scalp Care - Olive and Tea Tree Oil Co-Wash

16 OZ (454g)

NDC 72474-103-01